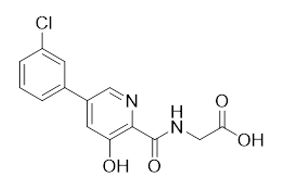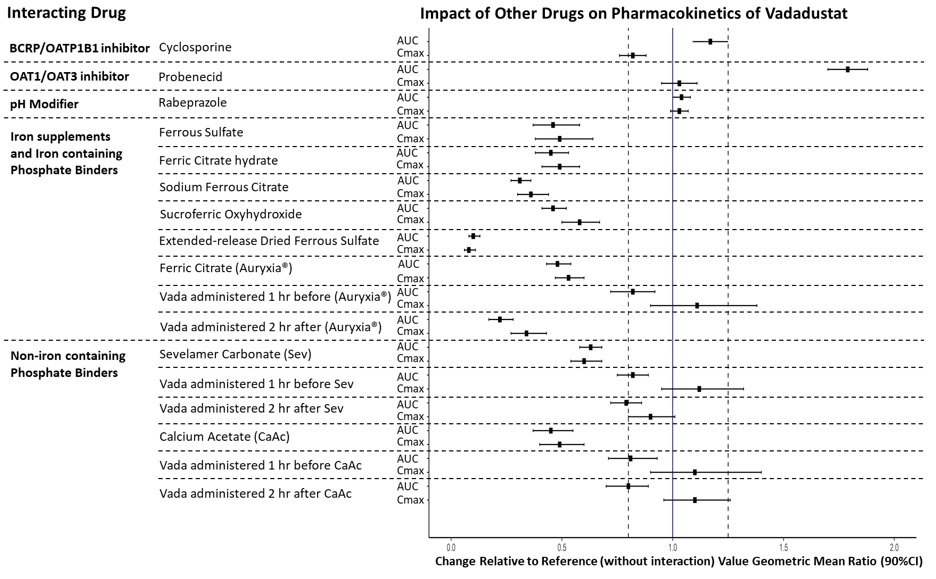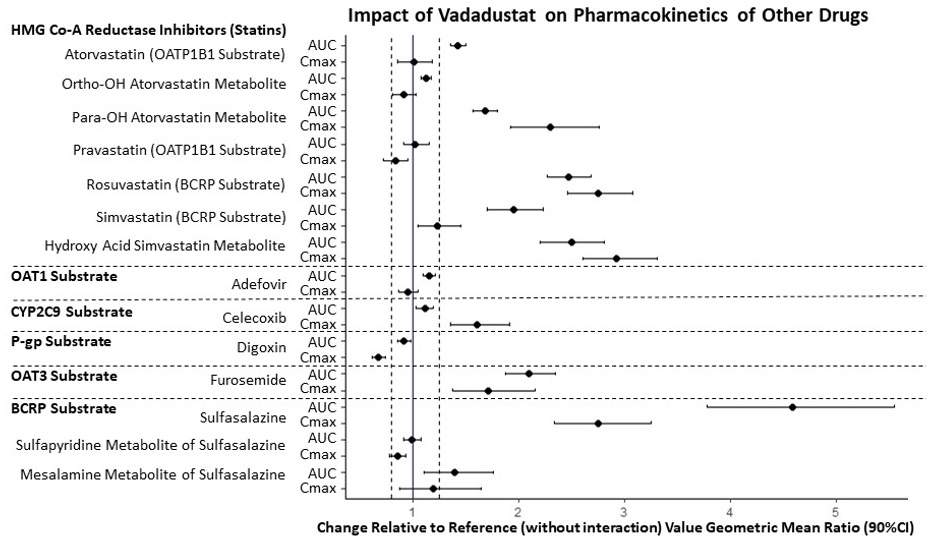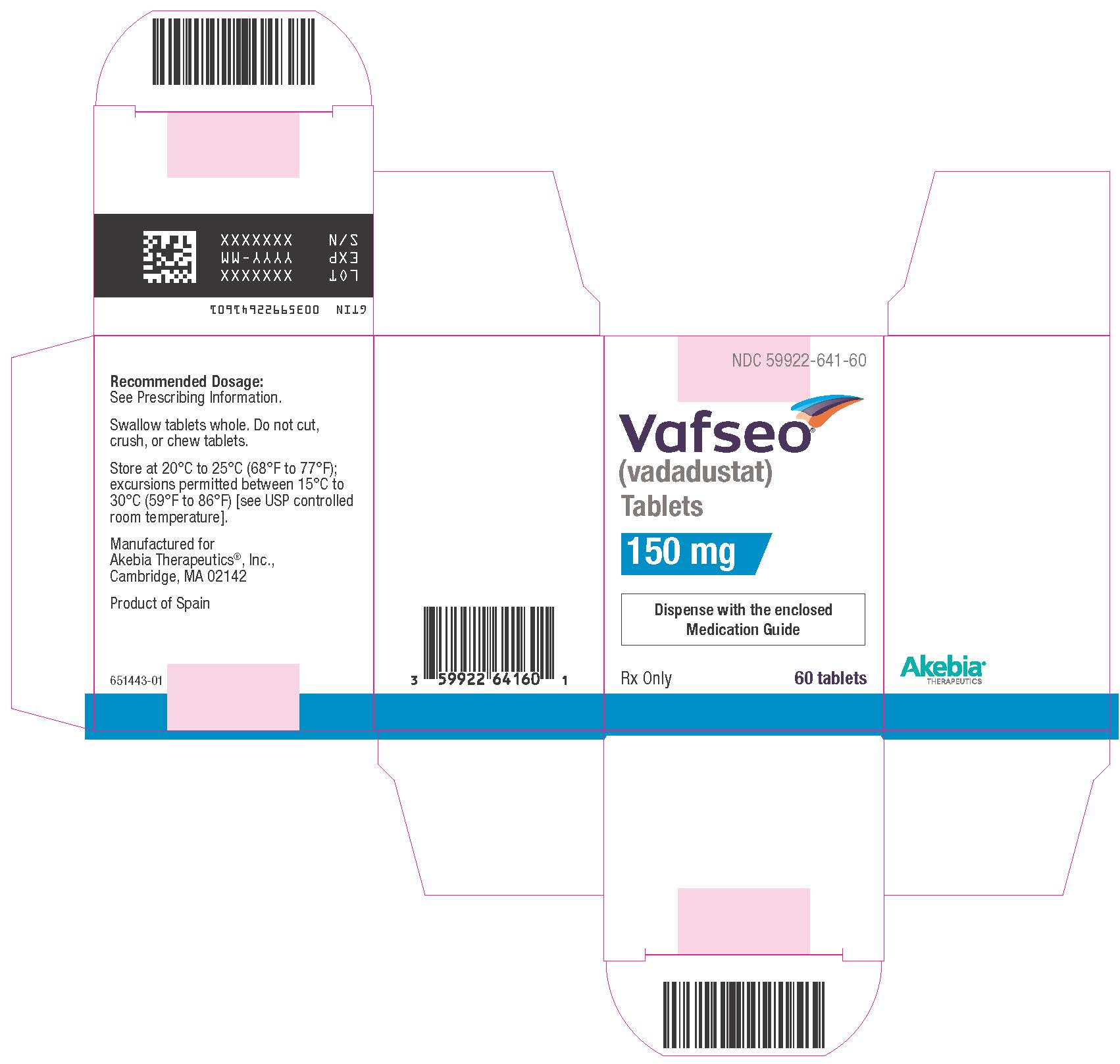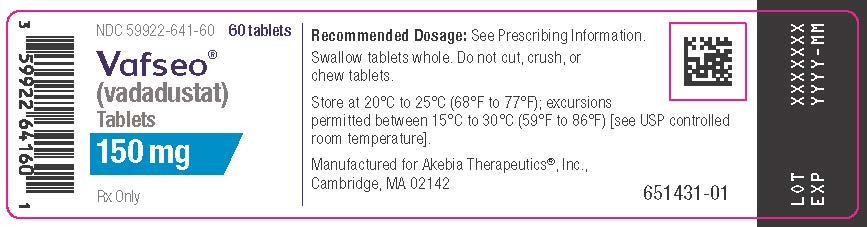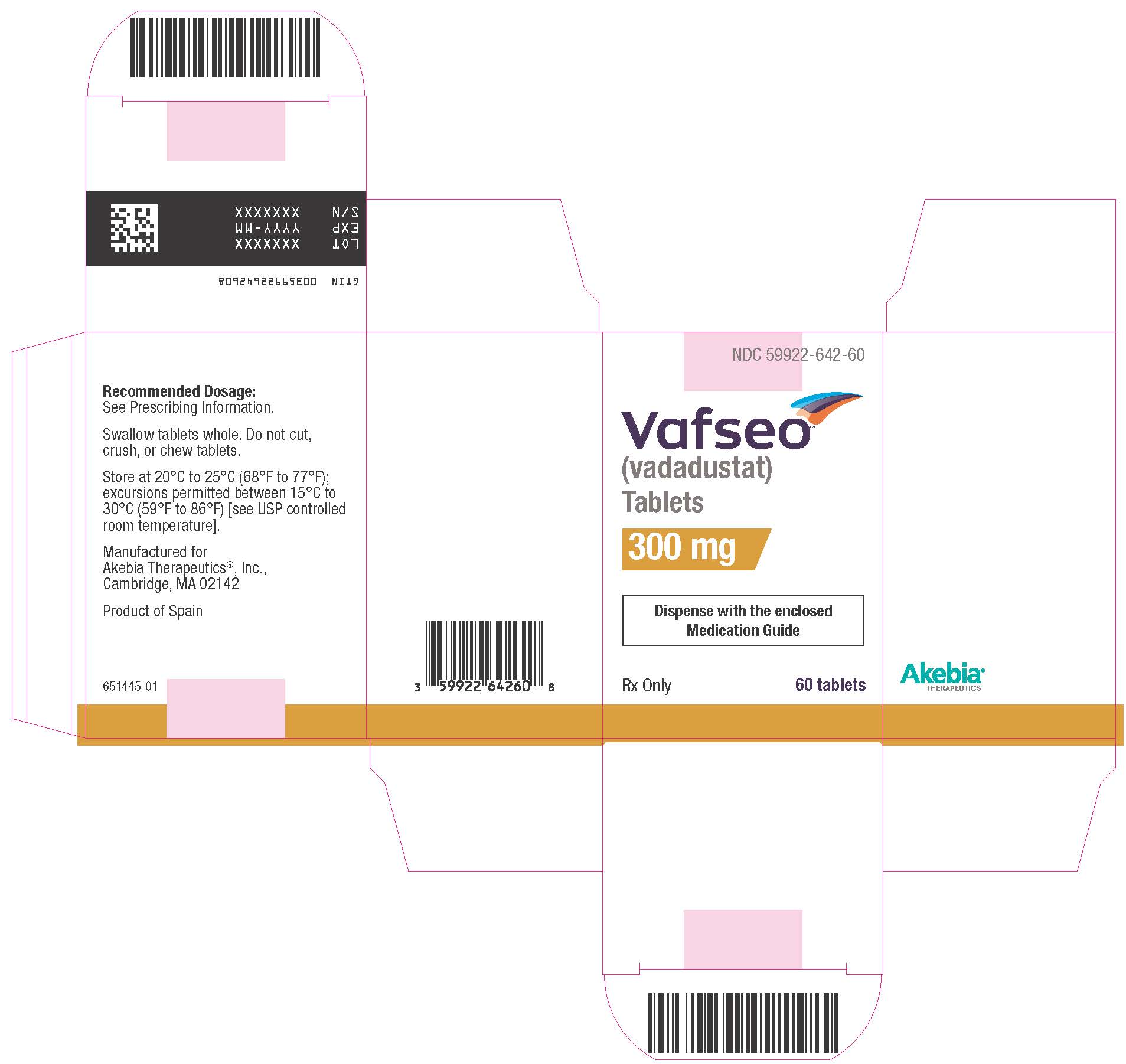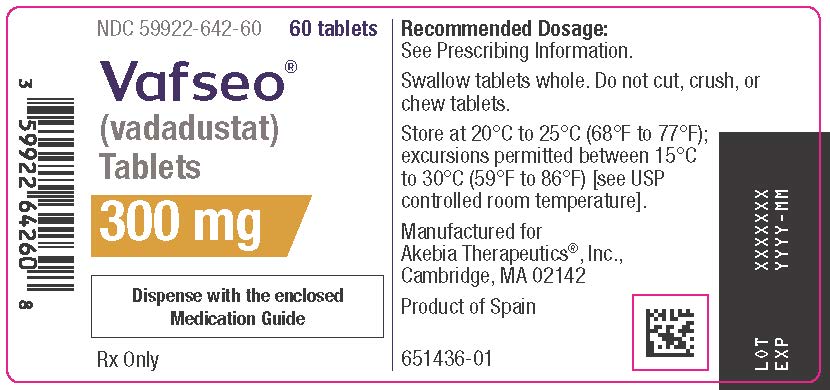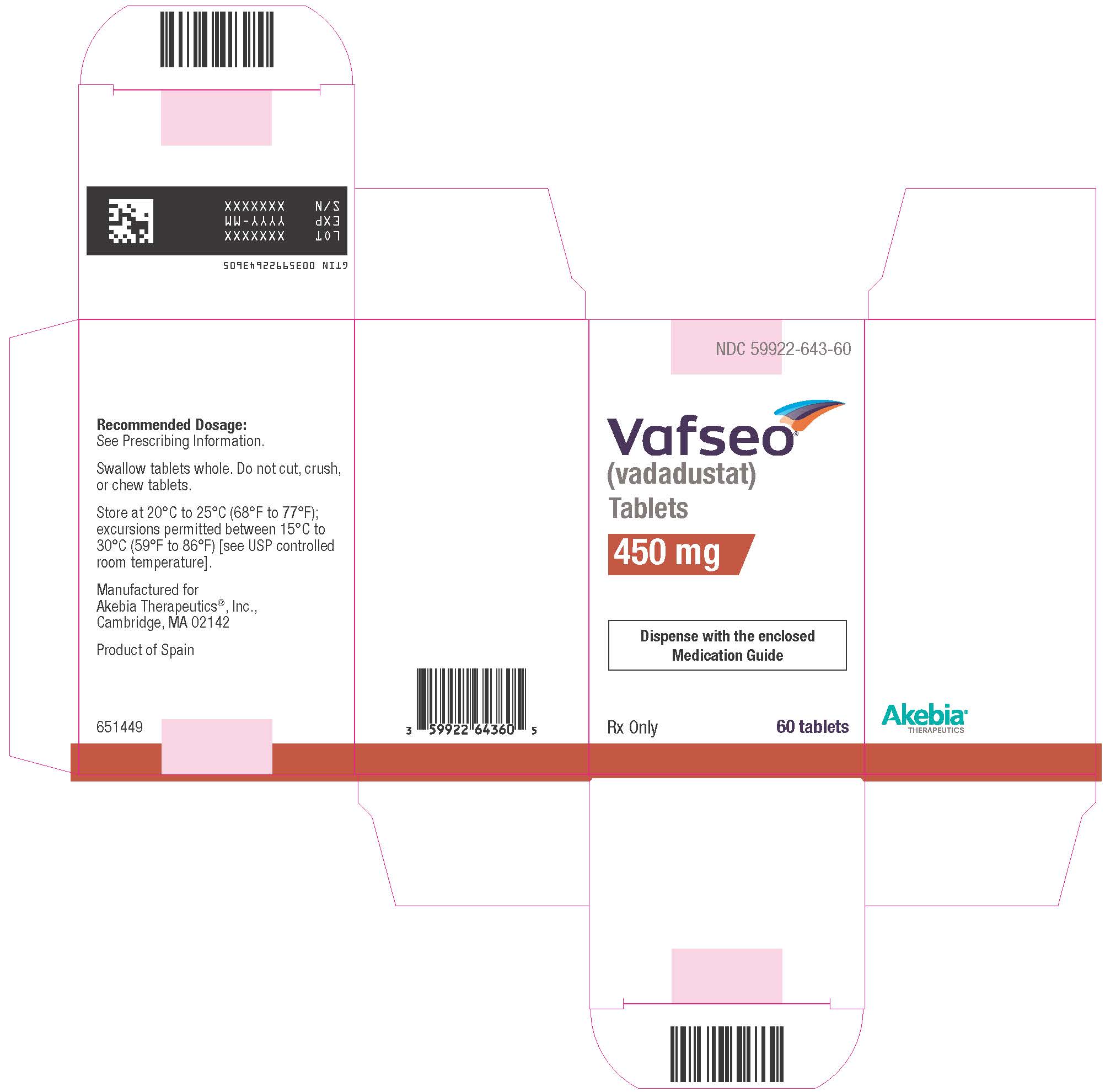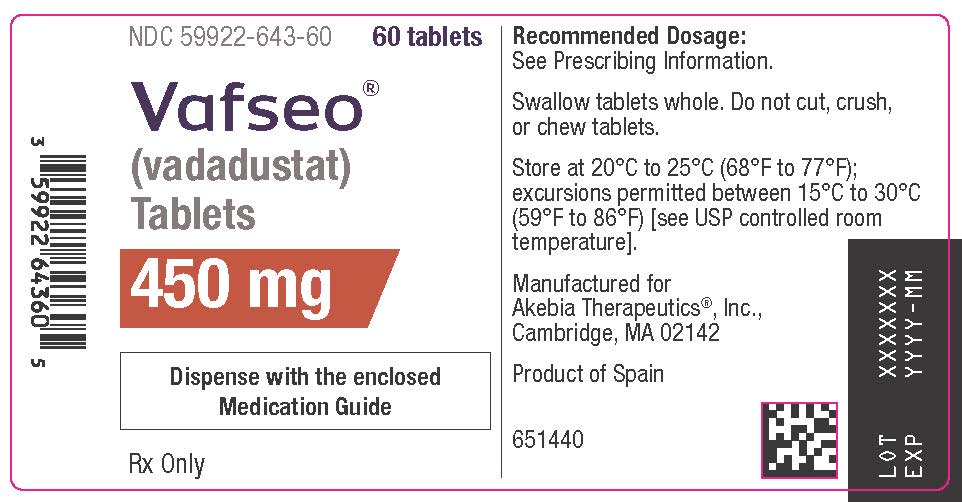 DRUG LABEL: VAFSEO
NDC: 59922-641 | Form: TABLET, FILM COATED
Manufacturer: Akebia Therapeutics, Inc.
Category: prescription | Type: HUMAN PRESCRIPTION DRUG LABEL
Date: 20240331

ACTIVE INGREDIENTS: VADADUSTAT 150 mg/1 1

HIGHLIGHTS OF PRESCRIBING INFORMATION

These highlights do not include all the information needed to use VAFSEO safely and effectively. See full prescribing information for VAFSEO.
VAFSEO® (vadadustat) tablets, for oral use
Initial U.S. Approval: 2024

WARNING: INCREASED RISK OF DEATH, MYOCARDIAL INFARCTION, STROKE, VENOUS THROMBOEMBOLISM, AND THROMBOSIS OF VASCULAR ACCESS

See full prescribing information for complete boxed warning.

- VAFSEO increases the risk of thrombotic vascular events, including major adverse cardiovascular events (MACE). (5.1)
- Targeting a hemoglobin level greater than 11 g/dL is expected to further increase the risk of death and arterial and venous thrombotic events, as occurs with erythropoietin stimulating agents (ESAs), which also increase erythropoietin levels. (5.1)
- No trial has identified a hemoglobin target level, dose of VAFSEO, or dosing strategy that does not increase these risks. (2.4)
- Use the lowest dose of VAFSEO sufficient to reduce the need for red blood cell transfusions. (2.4)

1 INDICATIONS AND USAGE

VAFSEO is a hypoxia-inducible factor prolyl hydroxylase (HIF PH) inhibitor indicated for the treatment of anemia due to chronic kidney disease (CKD) in adults who have been receiving dialysis for at least three months. (1)

Limitations of Use
Not been shown to improve quality of life, fatigue, or patient well-being.
Not indicated for use:

- As a substitute for transfusion in patients requiring immediate correction of anemia. (1)
- In patients with anemia due to CKD not on dialysis. (1, 5.6)

2 DOSAGE AND ADMINISTRATION

- Recommended starting dose is 300 mg orally once daily, with or without food. (2.3)
- Monitor hemoglobin levels when initiating or adjusting dose and then monthly. (2.1 and 2.4)
- Increase the dose no more frequently than once every 4 weeks. Decreases in dose can occur more frequently. (2.4)
- Adjust dose in increments of 150 mg to achieve or maintain hemoglobin levels of 10 g/dL to 11 g/dL. Doses may range from 150 mg to a maximum of 600 mg. (2.4)

3 DOSAGE FORMS AND STRENGTHS

- Tablets: 150 mg, 300 mg and 450 mg (3)

4 CONTRAINDICATIONS

- Known hypersensitivity to VAFSEO or any of its components (4)
- Uncontrolled hypertension (4)

5 WARNINGS AND PRECAUTIONS

- Hepatotoxicity: Has been reported in patients taking VAFSEO. Measure ALT, AST and bilirubin prior to the initiation of VAFSEO, monthly after initiation for the first 6 months, then as clinically indicated. Discontinue VAFSEO if ALT or AST is persistently elevated or accompanied by elevated bilirubin. (5.2)
- Hypertension: Worsening hypertension, including hypertensive crisis may occur. Monitor blood pressure. Adjust anti-hypertensive therapy as needed. (5.3)
- Seizures: Seizures have occurred in patients with CKD taking VAFSEO. Monitor for new-onset seizures, premonitory symptoms, or change in seizure frequency. (5.4)
- Gastrointestinal Erosion: Gastric or esophageal erosions and gastrointestinal bleeding have been reported. (5.5)
- Malignancy: May have unfavorable effects on cancer growth. Not recommended if active malignancy. (5.7)

6 ADVERSE REACTIONS

The most common adverse reactions (occurring at ≥ 10%) were hypertension and diarrhea. (6.1).

To report SUSPECTED ADVERSE REACTIONS, contact Akebia Therapeutics, Inc. at 1-844-445-3799 or FDA at 1-800-FDA-1088 or www.fda.gov/medwatch.

7 DRUG INTERACTIONS

- Iron supplements and iron-containing phosphate binders: Administer VAFSEO at least 1 hour before products containing iron. (7.1)
- Non-iron-containing phosphate binders: Administer VAFSEO at least 1 hour before or 2 hours after non-iron-containing phosphate binders. (7.1)
- BCRP substrates: Monitor for signs of substrate adverse reactions and consider substrate dose reduction. (7.2)
- Statins: Monitor for statin-related adverse reactions (7.2).

8 USE IN SPECIFIC POPULATIONS

- Pregnancy: May cause fetal harm. (8.1)
- Lactation: Breastfeeding not recommended until two days after the final dose. (8.2)
- Hepatic Impairment: Not recommended for use in patients with cirrhosis or active, acute liver disease. (8.6)

FULL PRESCRIBING INFORMATION

WARNING: INCREASED RISK OF DEATH, MYOCARDIAL INFARCTION, STROKE, VENOUS THROMBOEMBOLISM, AND THROMBOSIS OF VASCULAR ACCESS

VAFSEO increases the risk of thrombotic vascular events, including major adverse cardiovascular events (MACE) [see Warnings and Precautions (5.1)].

Targeting a hemoglobin level greater than 11 g/dL is expected to further increase the risk of death and arterial and venous thrombotic events, as occurs with erythropoietin stimulating agents (ESAs), which also increase erythropoietin levels [see Warnings and Precautions (5.1)].

No trial has identified a hemoglobin target level, dose of VAFSEO, or dosing strategy that does not increase these risks [see Dosage and Administration (2.4)].

Use the lowest dose of VAFSEO sufficient to reduce the need for red blood cell transfusions [see Dosage and Administration (2.4)].

1 INDICATIONS AND USAGE

VAFSEO is indicated for the treatment of anemia due to chronic kidney disease (CKD) in adults who have been receiving dialysis for at least three months.

Limitations of Use

- VAFSEO has not been shown to improve quality of life, fatigue, or patient well-being.
- VAFSEO is not indicated for use:
  - As a substitute for red blood cell transfusions in patients who require immediate correction of anemia
  - In patients with anemia due to CKD not on dialysis [see Warnings and Precautions (5.6)].

2 DOSAGE AND ADMINISTRATION

2.1 Pre-Treatment and On-Treatment Evaluations of Anemia, Iron Stores, and Liver Tests

Evaluation of Anemia and Iron Stores
Correct and exclude other causes of anemia (e.g., vitamin deficiency, metabolic or chronic inflammatory conditions, bleeding) before initiation of VAFSEO. Evaluate iron status in all patients before and during treatment. Administer supplemental iron therapy when serum ferritin is less than 100 mcg/L or when serum transferrin saturation is less than 20%. The majority of patients with CKD will require supplemental iron during the course of therapy.

Measure hemoglobin (Hb) at baseline and as recommended in section 2.4.

Liver Testing
Measure serum alanine aminotransferase (ALT), aspartate aminotransferase (AST) and bilirubin prior to the initiation of VAFSEO and monthly after initiation for the first 6 months and then monitor as clinically indicated [see Warnings and Precautions (5.2)].

Discontinue VAFSEO if there are persistent ALT or AST elevations greater than 3 times upper limit of normal (ULN) or if ALT or AST elevations greater than 3 times ULN are accompanied by a bilirubin increase greater than 2 times ULN [see Warnings and Precautions (5.2)].

2.2 Important Dosing Information

Individualize dosing and use the lowest dose of VAFSEO sufficient to reduce the need for red blood cell transfusions. Do not target a hemoglobin level higher than 11 g/dL.

VAFSEO can be taken with or without food.

VAFSEO should be swallowed whole. Tablets should not be cut, crushed, or chewed.

VAFSEO can be administered without regard to the timing or type of dialysis [see Clinical Pharmacology (12.3)].

If a dose of VAFSEO is missed, it should be taken as soon as possible, unless it is the same day as the next dose. In this case, the missed dose should be skipped, and the next dose taken at the usual time. Double doses should not be taken to make-up for a missed dose.

2.3 Recommended Starting Dose of VAFSEO

Adults Not Being Treated with an ESA
The recommended starting dose is 300 mg orally once daily.

Adults Being Switched from an ESA
When converting from an ESA to VAFSEO, the recommended starting dose is 300 mg orally once daily.

Taking into account the gradual rise in Hb with VAFSEO, red blood cell (RBC) transfusions or ESA treatment may be considered during the transition phase if Hb values fall below 9 g/dL or Hb response is considered not acceptable. Patients receiving RBC transfusions should continue VAFSEO treatment during the transfusion period. VAFSEO should be paused for those patients receiving temporary ESA rescue treatment and may be resumed when Hb levels are greater than or equal to 10 g/dL. Depending on the ESA used for rescue, the pause in VAFSEO treatment should be extended to:

- 2 days after the last dose of epoetin
- 7 days after the last dose of darbepoetin alfa
- 14 days after the last dose of methoxy polyethylene glycol-epoetin beta.

Following ESA rescue, VAFSEO should be resumed at the prior dose or with a dose that is 150 mg greater than the prior dose, with subsequent titration according to the dose titration guidelines given below in this section.

2.4 Monitoring Response to Therapy and Dose Adjustment

Following initiation of therapy and after each dose adjustment, monitor hemoglobin (Hb) levels, every two weeks until stable, then monitor at least monthly [see Warnings and Precautions (5.1)].

Dose Titration
Increase the dose no more frequently than once every 4 weeks. Decreases in dose can occur more frequently.

Adjust dose in increments of 150 mg to achieve or maintain Hb levels within 10 g/dL to 11 g/dL. Doses may range from 150 mg to a maximum of 600 mg. When adjusting the dose, consider the patient’s Hb variability, Hb rate of rise and rate of decline, and VAFSEO responsiveness. A single Hb excursion may not require a dosing change.

- If the Hb rises rapidly (e.g., more than 1 g/dL in any 2-week period or more than 2 g/dL in 4 weeks), interrupt or reduce the dose.
- If the Hb level exceeds 11 g/dL, interrupt the dose of VAFSEO until Hb is less than or equal to 11 g/dL then resume with a dose that is 150 mg less than the dose prior to interruption.
- Treatment with VAFSEO should not be continued beyond 24 weeks of therapy if a clinically meaningful increase in Hb level is not achieved. Alternative explanations for an inadequate response should be sought and treated before re-starting therapy.

2.5 Dosage Adjustments Due to Drug Interactions

Oral Iron and Phosphate Binders
VAFSEO should be administered at least 1 hour before dosing oral iron supplements, products containing iron, or iron-containing phosphate binders [see Drug Interactions (7.1)].

VAFSEO should be administered at least 1 hour before or 2 hours after dosing non-iron-containing phosphate binders [see Drug Interactions (7.1)].

3 DOSAGE FORMS AND STRENGTHS

VAFSEO is available as a film-coated, immediate-release tablet in the following strengths:

Tablet Strength | Tablet Shape/Color | Tablet Markings
150 mg | round/white | “VDT” and “150”
300 mg | oval/yellow | “VDT” and “300”
450 mg | oval/pink | “VDT” and “450”

4 CONTRAINDICATIONS

VAFSEO is contraindicated in patients:

- with a known hypersensitivity to VAFSEO or any of its components [see Description (11)].
- with uncontrolled hypertension [see Warnings and Precautions (5.3)].

5 WARNINGS AND PRECAUTIONS

5.1 Increased Risk of Death, Myocardial Infarction (MI), Stroke, Venous Thromboembolism, and Thrombosis of Vascular Access

VAFSEO increases the risk of arterial and venous thrombotic events, that may be fatal, including myocardial infarction, stroke, venous thromboembolism and vascular access thrombosis [see Boxed Warning, Adverse Reactions (6.1)]. Patients with cardiovascular or cerebrovascular disease are at increased risk of these events. Avoid use in patients with a history of myocardial infarction, cerebrovascular event, or acute coronary syndrome within the 3 months prior to starting VAFSEO.

A rate of hemoglobin rise of greater than 1 g/dL over 2 weeks may contribute to these risks. Targeting a hemoglobin level of greater than 11 g/dL is expected to further increase the risk of death and arterial and venous thrombotic events, as occurs with ESAs, which also increase erythropoietin levels.

No trial has identified a hemoglobin target level, dose of VAFSEO, or dosing strategy that does not increase these risks. Use the lowest dose of VAFSEO sufficient to reduce the need for red blood cell transfusions. Adherence to dosing and hemoglobin monitoring recommendations is important to avoid excessive erythropoiesis [see Dosage and Administration (2.4)].

Advise patients to seek immediate medical attention if they develop signs or symptoms of myocardial infarction, stroke, venous thromboembolism, or thrombosis of vascular access. Evaluate and manage promptly if these occur.

5.2 Hepatotoxicity

VAFSEO may cause hepatotoxicity. In clinical trials, hepatocellular injury attributed to VAFSEO was reported in less than 1% of patients, including one case of severe hepatocellular injury with jaundice. All events were asymptomatic and resolved after discontinuation of VAFSEO. The time to onset was generally within the first 3 months of treatment.

Elevated serum ALT, AST, and bilirubin were seen in 1.8%, 1.8% and 0.3% of CKD patients treated with VAFSEO, respectively.

Measure ALT, AST and bilirubin prior to the initiation of VAFSEO and monthly after initiation for the first 6 months and then monitor as clinically indicated [see Dosage and Administration (2.1)].

Discontinue VAFSEO if there is persistent ALT or AST greater than 3 times ULN or if ALT or AST elevations greater than 3 times upper limit of normal (ULN) are accompanied by a bilirubin increase greater than 2 times ULN.

VAFSEO is not recommended in patients with cirrhosis or active, acute liver disease.

5.3 Hypertension

VAFSEO is contraindicated in patients with uncontrolled hypertension. In the INNO2VATE-1 and INNO2VATE-2 clinical trials, worsening of hypertension was reported in 14% (9.4 per 100 person-years [PY]) of patients receiving VAFSEO and 17% (11.8 per 100 PY) of patients receiving darbepoetin alfa. Serious worsening of hypertension was reported in 2.7% (1.7 per 100 PY) of patients receiving VAFSEO and 3% (1.8 per 100 PY) of patients receiving darbepoetin alfa. Cases of hypertensive crisis including hypertensive encephalopathy and seizures have also been reported in patients receiving VAFSEO. Periodically monitor blood pressure and adjust or initiate anti-hypertensive therapy as needed.

5.4 Seizures

Seizures have occurred in patients treated with VAFSEO. In the INNO2VATE-1 and INNO2VATE-2 clinical trials, seizures occurred in 1.6% (1.0 per 100 PY) of patients who received VAFSEO and 1.6% (1.0 per 100 PY) of patients who received darbepoetin alfa. Following initiation of VAFSEO, monitor patients closely for premonitory neurologic symptoms. Advise patients to contact their healthcare practitioner for new-onset seizures, premonitory symptoms, or change in seizure frequency.

5.5 Gastrointestinal Erosion

In the INNO2VATE-1 and INNO2VATE-2 clinical trials, gastric or esophageal erosions occurred in 6.4% (4.0 per 100 PY) of patients receiving VAFSEO and 5.3% (3.3 per 100 PY) of darbepoetin alfa-treated patients. Serious gastrointestinal erosions, including gastrointestinal bleeding and the need for red blood cell transfusions were reported in 3.4% (2.1 per 100 PY) and 3.3% (2.0 per 100 PY) of those receiving VAFSEO and darbepoetin alfa, respectively. Consider this risk particularly in patients at increased risk for gastrointestinal erosions, such as those with a history of gastrointestinal erosion, peptic ulcer disease, use of concomitant medications that increase the risk of gastrointestinal erosion, and current tobacco smokers and alcohol drinkers.

Advise patients of the symptoms and signs of gastric and esophageal erosions and of gastrointestinal bleeding and to seek prompt medical care if these occur.

5.6 Serious Adverse Reactions in Patients with Anemia Due to Chronic Kidney Disease and Not on Dialysis

The safety of VAFSEO has not been established for the treatment of anemia due to CKD in adults not on dialysis and its use is not recommended in this setting [see Indications and Usage (1)].

In large clinical trials in adults with anemia of CKD who were not on dialysis (PRO2TECT-1 and PRO2TECT-2), an increased risk of mortality, stroke, myocardial infarction, serious acute kidney injury, serious hepatic injury, and serious gastrointestinal erosions was observed in patients treated with VAFSEO compared to darbepoetin alfa.

5.7 Malignancy

Because increased hypoxia inducible factor (HIF)-1 levels may be associated with unfavorable effects on cancer growth, VAFSEO has not been studied and is not recommended in patients with active malignancies. In the INNO2VATE-1 and INNO2VATE-2 clinical trials, malignancies were observed in 2.2% (1.3 per 100 PY) of patients treated with VAFSEO and 3.0% (1.8 per 100 PY) of patients treated with darbepoetin alfa. No evidence of increased carcinogenicity was observed in animal studies [see Nonclinical Toxicology (13.1)].

6 ADVERSE REACTIONS

The following clinically significant adverse reactions are discussed elsewhere in the labeling:

- Increased risk of death, myocardial infarction, stroke and venous thromboembolism, and thrombosis of vascular access [see Boxed Warning and Warnings and Precautions (5.1)]
- Hepatotoxicity [see Warnings and Precautions (5.2)]
- Hypertension [see Warnings and Precautions (5.3)]
- Seizures [see Warnings and Precautions (5.4)]
- Gastrointestinal erosion [see Warnings and Precautions (5.5)]
- Serious adverse reactions in patients with anemia due to chronic kidney disease and not on dialysis [see Warnings and Precautions (5.6)]

6.1 Clinical Trials Experience

Because clinical trials are conducted under widely varying conditions, adverse reaction rates observed in the clinical trials of a drug cannot be directly compared to rates in the clinical trials of another drug and may not reflect the rates observed in practice.

The safety of VAFSEO was evaluated in adults with dialysis-dependent chronic kidney disease (DD-CKD) with anemia in the INNO2VATE-1 and INNO2VATE-2 trials [see Clinical Studies (14.1)]. Both trials randomized patients to VAFSEO or darbepoetin alfa. Results in this section are based on the pooled VAFSEO treatment arms and pooled darbepoetin alfa arms from these trials.

There were 1947 patients treated with VAFSEO and 1955 patients treated with darbepoetin alfa. In the pooled VAFSEO treatment arm, 71% of the participants were treated continuously for at least 6 months of VAFSEO and 44% of participants received VAFSEO for at least 1 year.

VAFSEO was non-inferior to darbepoetin alfa on the time to first occurrence of major adverse cardiovascular events (MACE) in adults with anemia due to CKD who were on dialysis [see Clinical Studies (14.1)].

Permanent treatment discontinuation due to an adverse reaction was reported in 4.9% of patients treated with VAFSEO and 1.1% of patients treated with darbepoetin alfa. Gastrointestinal symptoms (nausea, vomiting and diarrhea) resulted in permanent treatment discontinuation in 1.8% of patients treated with VAFSEO.

The most common adverse reactions (>10% of VAFSEO-treated patients) were hypertension and diarrhea.

Table 1 lists the adverse reactions that occurred in at least 5% or greater of patients with DD-CKD treated with VAFSEO.

Table 1 Adverse Reactions (≥5%) in Patients with DD-CKD During INNO2VATE-1 and INNO2VATE-2

Adverse Reactions | VAFSEO N=1947 (%) | Darbepoetin Alfa N=1955 (%)
Hypertension* | 14 | 17
Diarrhea* | 13 | 10
Headache* | 9 | 8
Nausea* | 8 | 8
Fatigue* | 8 | 5
Abdominal pain* | 7 | 7
Vomiting* | 7 | 7
Gastrointestinal erosion* | 6 | 5
Dizziness* | 6 | 5
Dyspnea* | 6 | 7
Arteriovenous fistula thrombosis | 6 | 5
Dialysis related complication | 5 | 7
*Grouped Terms
Hypertension includes hypertensive crisis, pre-eclampsia and hypertensive encephalopathy.
Headache includes occipital neuralgia.
Fatigue includes asthenia, lethargy and malaise.
Vomiting includes hematemesis.
Gastrointestinal erosion includes duodenal ulcers and perforation, gastrointestinal ulcers and perforation, esophageal ulcers and perforation, and unspecified site or hematemesis, gastrointestinal hemorrhage, helicobacter duodenitis and gastritis, melaena, and gastric hemorrhage.
Dizziness includes labyrinthitis, vertigo, vestibular neuronitis and presyncope.
Dyspnea includes orthopnea and respiratory distress.

Adjudicated fatal and non-fatal thrombotic vascular events were observed in 9.0 per 100 PY of patients in the pooled VAFSEO arm and in 8.7 per 100 PY of patients in the pooled darbepoetin alfa (see Table 2).

Table 2 Adjudicated Thrombotic Vascular Events in Patients with DD-CKD (Fatal and Non-fatal Events)*

Event | VAFSEO (N = 1947) | Darbepoetin Alfa (N = 1955)
Event | Rate per 100 PY** | Rate per 100 PY**
Vascular access thrombosis | 4.8 | 3.9
Myocardial infarction | 2.9 | 2.8
Stroke | 1.1 | 1.4
Deep vein thrombosis | 0.5 | 0.6
Pulmonary embolism | 0.2 | 0.3
Arterial thrombosis | 0.2 | 0.1
PY = Person Years
*These data are not an adequate basis for comparison of rates between the study drug and active control.
** Based on time to first event analysis.

7 DRUG INTERACTIONS

7.1 Effect of Other Drugs on VAFSEO

Table 3 describes clinically significant drug interactions where concomitant use of another drug affects VAFSEO.

Table 3 Drug Interactions with VAFSEO that Affect Vadadustat Exposure

Iron supplements and phosphate binders
Clinical Effect | Co-administration with oral iron supplements, products containing iron, or phosphate binders decreases the exposure of vadadustat [see Clinical Pharmacology (12.3)], which may reduce the effectiveness of VAFSEO.
Prevention or Management | Stagger administration when VAFSEO is used with oral iron supplements, products containing iron, iron-containing phosphate binders, or non-iron-containing phosphate binders [see Dosage and Administration (2.5)].
Examples* | Iron supplements: ferric citrate, ferrous sulfate, sodium ferrous citrate Iron-containing phosphate binders: ferric citrate, sucroferric oxyhydroxide Non-iron-containing phosphate binders: calcium acetate, sevelamer carbonate
Organic anion transporter (OAT) OAT1/OAT3 inhibitors
Clinical Effect | Co-administration with OAT1/OAT3 (Organic Anion Transporter) inhibitors may increase the area under the concentration curve (AUC) of vadadustat [see Clinical Pharmacology (12.3)], which may increase the risk of VAFSEO adverse reactions.
Prevention or Management | Closely monitor for too large or too rapid an increase in Hb response and for adverse reactions.
Examples* | OAT1 inhibitors: probenecid, rifampicin OAT3 inhibitors: gemfibrozil, probenecid, teriflunomide
*These examples are not a comprehensive list of all possible drugs that may fit this category.

7.2 Effect of VAFSEO on Other Drugs

Table 4 describes clinically significant drug interactions where VAFSEO affects the co-administered drug.

Table 4 Drug Interactions with VAFSEO that affect co-administered drugs

BCRP substrates
Clinical Effect | Vadadustat may increase the exposure of BCRP substrates [see Clinical Pharmacology (12.3)], which may increase the risk of adverse reactions related to the BCRP substrate.
Prevention or Management | Monitor for signs of adverse effects of the co-administered BCRP substrate and reduce substrates’ dosage in accordance with their approved product labeling, if needed.
Example* | sulfasalazine

Statins
Clinical Effect | Vadadustat increases the maximal concentration (Cmax) and AUC of some statins when co-administered [see Clinical Pharmacology (12.3)].
Prevention or Management | Monitor for possible statin-related adverse reactions.
Prevention or Management | Concomitant Drug Name | Recommendation
Prevention or Management | Simvastatin | Starting dose of simvastatin should be 5 mg/day.
Prevention or Management | Simvastatin | Maximum daily dose of simvastatin not to exceed 20 mg.
Prevention or Management | Rosuvastatin | Maximum daily dose of rosuvastatin not to exceed 5 mg.

OAT3 substrates
Clinical Effect | Vadadustat may increase the exposure of co-administered OAT3 substrates [see Clinical Pharmacology (12.3)], which may increase the risk of adverse reactions related to these substrates.
Prevention or Management | Monitor for signs of adverse reactions of the co-administered OAT3 substrates and adjust substrates’ dosage in accordance with their approved product labeling, if needed.
Examples* | cefaclor, ceftizoxime, famotidine, furosemide, oseltamivir carboxylate, penicillin G, sitagliptin
*These examples are not a comprehensive list of all possible drugs that may fit this category.

8 USE IN SPECIFIC POPULATIONS

8.1 Pregnancy

Risk Summary
Available data with VAFSEO use in pregnant women are insufficient to establish a drug-associated risk of major birth defects, miscarriage, or adverse maternal or fetal outcomes. There are risks to the mother and fetus associated with CKD (see Clinical Considerations). Vadadustat administration orally to pregnant rats and rabbits during the period of organogenesis was associated with reduced fetal weight at doses that caused maternal toxicity. In rat and rabbit studies, vadadustat was not teratogenic (see Data).

The background risk of major birth defects and miscarriage for the indicated population is unknown. All pregnancies have a background risk of birth defect, loss, or other adverse outcomes. In the U.S. general population, the estimated background risks of major birth defects and miscarriage in clinically recognized pregnancies is 2 to 4% and 15 to 20%, respectively. VAFSEO should only be used during pregnancy if the benefit justifies the potential risk to the fetus.

Clinical Considerations
Disease-Associated Maternal and/or Embryo/Fetal Risk: CKD in pregnancy increases the risk for maternal hypertension, preeclampsia, miscarriage, stillbirth, preterm delivery, low birth weight infants, and polyhydramnios.

Data
Animal Data
Vadadustat decreased fetal weight and reduced fetal skeletal ossification in rats at a dose of 160 mg/kg/day (1.7 times the maximum recommended human dose [MRHD] based on AUC), which was associated with maternal toxicity defined by reduced body weight gain and food consumption.

Vadadustat was orally administered to pregnant rabbits at doses of 10, 25, or 50 mg/kg/day from gestation day 6 until gestation day 18 during the period of organogenesis. Vadadustat administration at 50 mg/kg/day resulted in maternal toxicity of reduced body weight gain, but no adverse effects on embryofetal development were observed at doses less than or equal to 50 mg/kg/day (1.5 times the MRHD based on AUC).

In a pre- and postnatal development study, pregnant rats were dosed orally with vadadustat 20, 40, or 80 mg/kg/day from implantation until weaning (gestation day 6 to lactation day 20) at 20, 40, or 80 mg/kg/day. There were decreased body weights of offspring at the dose of 80 mg/kg/day but no adverse effects were observed at doses less than or equal to 80 mg/kg/day (0.3 times the MRHD based on AUC) in dams.

8.2 Lactation

Risk Summary
There are no data on the presence of vadadustat in human milk, the effects of vadadustat on the breastfed child, or the effects on milk production. Vadadustat is present in the milk of lactating rats (see Data). When a drug is present in animal milk, it is likely that the drug will be present in human milk. Given the serious adverse reactions seen in adults treated with VAFSEO, such as thrombotic vascular events, advise patients not to breastfeed during treatment with VAFSEO, and for 2 days after the final dose.

Data
Vadadustat was detected in the milk of lactating rats after a single oral administration of radiolabeled vadadustat at 50 mg/kg. The maximum ratio of milk to plasma concentration in rats was 14.5 at 8 hours postdose and the ratio of milk to plasma AUC was 6.

8.4 Pediatric Use

The safety and effectiveness of VAFSEO in pediatric patients have not been established.

8.5 Geriatric Use

There were 1330 patients 65 years of age and older in the pooled INNO2VATE-1 and INNO2VATE-2 clinical trials. Of the total number of VAFSEO-treated patients in these studies, 449 (23%) were 65 to 74 years of age, 194 (10%) were 75 to 84 years of age, and 24 (1%) were 85 years of age and older. No overall differences in safety or effectiveness were observed between patients 65 years of age and older and younger adult patients [see Clinical Studies (14.2)].

8.6 Hepatic Impairment

VAFSEO is not recommended in patients with cirrhosis or active, acute liver disease [see Warnings and Precautions (5.2)].

9 DRUG ABUSE AND DEPENDENCE

9.1 Controlled Substance

VAFSEO contains vadadustat, which is not a controlled substance.

9.2 Abuse

Drug abuse is intentional non-therapeutic use of a drug, even once, for its rewarding psychological or physiological effects. Abuse of VAFSEO may be seen in athletes for the effects on erythropoiesis.

Abuse-Related Adverse Reactions

There are no data on the abuse of VAFSEO in humans. Vadadustat and its metabolites neither selectively penetrate the central nervous system, nor produce behavioral effects in animals that are consistent with central nervous system activity.

Misuse of drugs that increase erythropoiesis, such as VAFSEO, by healthy persons may lead to polycythemia, which may be associated with life-threatening cardiovascular complications (e.g., stroke, myocardial infarction, and thromboembolism).

10 OVERDOSAGE

VAFSEO overdose may result in exaggeration of the pharmacologic effects such as increased Hb. VAFSEO overdose should be managed as clinically appropriate (e.g., reduction of VAFSEO dose or discontinuation). Approximately 16% of the vadadustat dose is removed by dialysis. There is no specific antidote.

11 DESCRIPTION

VAFSEO contains vadadustat, a hypoxia-inducible factor prolyl hydroxylase (HIF PH) inhibitor. Vadadustat is 2-[[5-(3-chlorophenyl)-3-hydroxypyridine-2-carbonyl]amino]acetic acid. Vadadustat has a molecular weight of 306.70. The empirical formula is C14H11ClN2O4.

The chemical structure is:

Vadadustat is a white to off-white solid that is practically insoluble in water.

Vadadustat is formulated as a film-coated, immediate-release tablet for oral administration.

VAFSEO is available in 150 mg, 300 mg and 450 mg strengths. Inactive ingredients include: colloidal silicon dioxide, hydroxypropyl methylcellulose, magnesium stearate, microcrystalline cellulose, and sodium starch glycolate. The tablet film-coating contains polyvinyl alcohol, polyethylene glycol (PEG) and talc.

Colorants include:
150 mg tablet - titanium dioxide
300 mg tablet - titanium dioxide and yellow iron oxide
450 mg tablet - titanium dioxide, iron oxide red and ferrosoferric oxide

12 CLINICAL PHARMACOLOGY

12.1 Mechanism of Action

Vadadustat is a reversible inhibitor of HIF-prolyl-4-hydroxylases (PH)1, PH2, and PH3 (IC50 in the nM range). This activity results in the stabilization and nuclear accumulation of HIF-1α and HIF-2α transcription factors, and increased production of erythropoietin (EPO).

12.2 Pharmacodynamics

After a single dose of vadadustat 80 to 1200 mg (0.27 to 4 times the approved recommended starting dosage) in healthy male adults, a dose-dependent increase in EPO was observed.

Cardiac Electrophysiology
At a dose of 600 mg or 1200 mg (2 or 4 times the approved recommended starting dosage), VAFSEO does not prolong the QTc interval to any clinically relevant extent.

12.3 Pharmacokinetics

Vadadustat AUC and observed peak concentration (Cmax) increased proportionally after single doses from 80 mg to 1200 mg (0.27 to 4 times the approved recommended starting dosage). Vadadustat is expected to reach steady state by day 3 following once daily dosing, with no significant accumulation.

Absorption
The time to peak plasma concentration (Tmax) of vadadustat is approximately 2 to 3 hours.

Effect of Food
No clinically significant differences in vadadustat pharmacokinetics were observed following administration of a high-fat meal.

Distribution
Protein binding of vadadustat is ≥99.5% in human plasma. Vadadustat does not distribute into red blood cells.

Elimination
The mean half-life of vadadustat in patients on chronic hemodialysis was 9.2 hours.

Metabolism
Vadadustat is primarily metabolized via glucuronidation by UDP-glucuronosyltransferase (UGT) enzymes.

Excretion
After a single radiolabeled oral dose to healthy adults, 85.9% of the total dose was recovered; 58.9% in urine (<1% of total dose unchanged); and 26.9% in feces (9% of total dose unchanged).

Specific Populations
There were no clinically significant differences in the pharmacokinetics of vadadustat based on age, sex, race/ethnicity, or moderate hepatic impairment (Child-Pugh Class B). The effect of severe hepatic impairment (Child-Pugh Class C) on the pharmacokinetics of vadadustat is unknown.

Patients with Renal Impairment
Vadadustat clearance decreased with decreasing renal function and exposures in DD-CKD were approximately 2-fold higher compared to healthy adults. In patients with Stage 5 DD-CKD, no significant differences in pharmacokinetics (Cmax, AUC or mean half-life) were observed when VAFSEO was administered 4 hours before dialysis or 2 hours after dialysis.

Drug Interaction Studies
The impact of co-administered drugs on vadadustat exposure was examined in several drug-drug interaction (DDI) studies in healthy adults. The change in vadadustat exposure with coadministration compared to VAFSEO alone is summarized in Figure 1.

Figure 1 Impact of Other Drugs on Pharmacokinetics of Vadadustat

BCRP: breast cancer resistance protein; CI: confidence interval; OAT: organic anion transporter; OATP: organic anion-transporting polypeptide. The solid vertical line represents geometric mean ratio of 1 and dotted vertical lines represent the 0.80 to 1.25 boundary.

The impact of vadadustat on the exposure of other drugs was examined in several DDI studies in healthy adults. The change in drug exposure when coadministered with VAFSEO compared to the drug alone is summarized in Figure 2.

Figure 2 Effect of Vadadustat on Pharmacokinetics of Other Drugs

BCRP: breast cancer resistance protein; CI: confidence interval; OAT: organic anion transporter; OATP: organic anion-transporting polypeptide. The solid vertical line represents geometric mean ratio of 1 and dotted vertical lines represent the 0.80 to 1.25 boundary.

13 NONCLINICAL TOXICOLOGY

13.1 Carcinogenesis, Mutagenesis, Impairment of Fertility

Vadadustat was not carcinogenic when administered orally at doses of 2, 7, and 20 mg/kg/day in a 6-month study in transgenic mice and at doses of 5, 15, and 50 mg/kg/day in a 2-year study in rats. The highest exposure to vadadustat in rats corresponds to 0.2 times the MRHD based on AUC.

Vadadustat was negative for mutagenicity in the in vitro bacterial reverse mutation assay. Vadadustat exhibited clastogenic activity in vitro but was negative in the in vivo chromosomal aberration assay in peripheral blood lymphocytes and comet assay in rats. Based on the weight of evidence, vadadustat is not considered genotoxic.

Fertility and early embryonic development toxicity studies were conducted in rats at dose levels of 40 to 120 mg/kg/day. Vadadustat did not impact fertility or reproduction in rats up to 80 mg/kg/day (1.5 times the MRHD based on AUC).

14 CLINICAL STUDIES

14.1 Treatment of Anemia Due to Chronic Kidney Disease in Adults on Dialysis

The efficacy and safety of VAFSEO given once daily for the treatment of anemia in adults with CKD on dialysis were demonstrated in two global, multi-center, randomized, active-controlled, non-inferiority, open-label trials in a total of 3923 patients with DD-CKD (INNO2VATE-1 and INNO2VATE-2). Patients in each trial were randomized 1:1 to receive VAFSEO with a starting dose of 300 mg once daily or darbepoetin alfa administered subcutaneously or intravenously as per the prescribing information for 52 weeks to assess the efficacy endpoints. VAFSEO was titrated in increments of 150 mg up to 600 mg to achieve the Hb target. After 52 weeks, patients continued study medication to assess long-term safety until the event-driven major adverse cardiovascular event (MACE) endpoints were reached. Efficacy in each study was based on the difference in mean change of Hb from baseline to the primary evaluation period (Weeks 24 to 36). An additional efficacy endpoint was the difference in mean change of Hb from baseline to the secondary evaluation period (Weeks 40 to 52). MACE was defined as all-cause mortality, non-fatal MI and non-fatal stroke and was evaluated in both trials.

The baseline Hb values were between 8 to 11 g/dL in the United States (US) and 9 to 12 g/dL outside the US. INNO2VATE-1 (NCT02865850) included patients with incident DD-CKD who initiated dialysis within 16 weeks prior to the beginning their trial participation and who were ESA-naive, had limited prior ESA use or were maintained on ESAs. INNO2VATE-2 (NCT02892149) included patients on chronic maintenance dialysis for more than 12 weeks who had converted from prior ESA therapy. In INNO2VATE-1, INNO2VATE-2, and the pooled INNO2VATE program the median and range of time from initiating dialysis to starting vadadustat was 0.1 (0.01 to 0.4), 2.7 (0.2 to 31.3) and 2.3 (0.01 to 31.3) years, respectively. The pooled population from the two trials had a range of 19 to 93 years of age, 55.9% were male, and the percentage of Caucasian, Hispanic, Black (including African Americans) and Asian patients was 64.5%, 38.5%, 24.1% and 4.5%, respectively. In both trials, VAFSEO was non-inferior to darbepoetin alfa in correcting and maintaining Hb levels across geographic-specific target Hb ranges [10 to 11 g/dL in the US and 10 to 12 g/dL outside the US] in adults with DD-CKD at weeks 24 to 36 and weeks 40 to 52.

Efficacy results are provided in Table 5. There were no apparent differences in response to VAFSEO across subgroups of age, gender, race and region.

Table 5 VAFSEO EFFICACY RESULTS: INNO2VATE TRIALS

 | INNO2VATE 1 |  | INNO2VATE 2
Hemoglobin (g/dL) | VAFSEO N = 181 | Darbepoetin Alfa N = 188 | VAFSEO N = 1777 | Darbepoetin Alfa N = 1777
Baseline Mean (SD) | 9.4 (1.1) | 9.2 (1.1) | 10.3 (0.9) | 10.2 (0.8)
Week 24 to 36 Mean (SD) | 10.4 (1.1) | 10.6 (0.9) | 10.4 (1.0) | 10.5 (1.0)
Adjusted LSM change from baseline [95% CI] | 1.3 [1.1, 1.5] | 1.6 [1.4, 1.8] | 0.2 [0.1, 0.3] | 0.4 [0.3, 0.4]
Treatment Difference [95% CI] VAFSEO – Darbepoetin Alfa | -0.3 [-0.5, -0.1] |  | -0.2 [-0.2, -0.1]
Week 40 to 52 Mean (SD) | 10.5 (1.2) | 10.6 (1.1) | 10.4 (1.0) | 10.6 (1.0)
Adjusted LSM Change from Baseline [95% CI] | 1.4 [1.2, 1.7] | 1.5 [1.2, 1.8] | 0.2 [0.2, 0.3] | 0.4 [0.3, 0.5]
Treatment Difference [95% CI] VAFSEO – Darbepoetin Alfa | -0.1 [-0.3, 0.2] |  | -0.2 [-0.3, -0.1]
CI: confidence interval; LSM: least squares mean; SD: standard deviation
A pre-specified non-inferiority margin of -0.75 g/dL was used to determine efficacy of VAFSEO.
The estimated treatment difference (VAFSEO – Darbepoetin Alfa) is obtained from an analysis of covariance (ANCOVA) model (treatment group, baseline Hb level, stratification factors [region and NYHA-CHF] as predictor variables) with multiple imputation.

Cardiovascular Outcomes - Patients with Dialysis-Dependent CKD
MACE was assessed in a combined analysis of INNO2VATE-1 and INNO2VATE-2. VAFSEO was non-inferior to darbepoetin alfa in time to first occurrence of MACE (Hazard Ratio 0.96; 95% CI 0.83, 1.11). Non-inferiority of VAFSEO was established because the upper bound of the 95% CI for the MACE hazard ratio was less than the pre-specified non-inferiority margin of 1.25. The results were consistent for the individual components of the MACE endpoint (see Table 6).

Table 6 Major Adverse Cardiovascular Events in the INNO2VATE Trials (ITT Analysesa)

 | VAFSEO N = 1947 PY=3134.4 | Darbepoetin Alfa N = 1955 PY=3164.0
First occurrence of MACE | 355 | 377
All-cause Mortality, n | 253 | 253
Non-fatal Myocardial Infarction, n | 76 | 87
Non-fatal Stroke, n | 26 | 37
MACE Hazard Ratiob (95% CI) | 0.96 (0.83, 1.11)
MACE Incidence Rate per 100 PY | 11.3 | 11.9
CI = Confidence interval; ITT = Intent to treat; MACE = Major adverse cardiovascular events; PY = Person Years
aITT analyses included events on and off treatment after randomization in patients who received at least one dose of study medication.
bAdjusted for baseline covariates

An analysis of the US region (N=2361 of 3902 total patients globally) for MACE and the individual MACE components, where patients were treated to a Hb target of 10 to 11 g/dL, showed a similar risk of MACE compared to darbepoetin alfa. The results were consistent for the individual components of the MACE endpoint (see Table 7).

Table 7 INNO2VATE Analyses of the MACE endpoint and the individual components for the US region where the patients were treated to a Hb target of 10 to 11 g/dL

 | VAFSEO N = 1180 PY=2119.6 | Darbepoetin Alfa N = 1181 PY=2133.7
First occurrence of MACE | 265 | 269
All-cause Mortality | 179 | 174
Non-fatal Myocardial Infarction | 68 | 69
Non-fatal Stroke | 18 | 26
MACE Hazard Ratioa (95% CI) | 1.00 (0.84, 1.18)
MACE Incidence rate per 100 PY | 12.5 | 12.6
CI = Confidence interval; ITT = Intent to treat; MACE = Major adverse cardiovascular events; PY = Person Years
aAdjusted for baseline covariates

16 HOW SUPPLIED/STORAGE AND HANDLING

How Supplied
VAFSEO film-coated tablets are available in the following strengths and packages:

Tablet Strength | Tablet Shape/Color | Tablet Markings | Pack size | NDC
150 mg | Round/white | “VDT” and “150” | 60 count bottle | 59922-641-60
300 mg | Oval/yellow | “VDT” and “300” | 60 count bottle | 59922-642-60
450 mg | Oval/pink | “VDT” and “450” | 60 count bottle | 59922-643-60

Storage and Handling

- Store at 20°C to 25°C (68°F to 77°F); excursions permitted between 15°C to 30°C (59°F to 86°F) [see USP controlled room temperature]. Keep out of reach of children.

17 PATIENT COUNSELING INFORMATION

Advise the patient to read the FDA-approved patient labeling (Medication Guide).

Inform patients:

Of the increased risk of death, myocardial infarction, stroke, and thromboembolism including vascular access thrombosis [see Warnings and Precautions (5.1)].

That hemoglobin levels will be monitored when initiating or adjusting therapy, every two weeks until stable, then at least monthly [see Warnings and Precautions (5.1)].

Of the risk of hepatotoxicity and that liver tests will be measured prior to the initiation of VAFSEO, monthly after initiation for the first 6 months, then as clinically indicated [see Warnings and Precautions (5.2)].

Of the risk of hypertension and advise patients of the importance to comply with antihypertensive therapy and monitoring of blood pressure [see Warnings and Precautions (5.3)].

Of the risk of seizures and advise patients to contact their healthcare provider for new-onset neurologic symptoms or change in seizure frequency [see Warnings and Precautions (5.4)].

Of the risk of gastrointestinal erosions and advise patients to contact their healthcare provider for signs and symptoms of gastric and esophageal erosions and of gastrointestinal bleeding [see Warnings and Precautions (5.5)].

Manufactured for: Akebia Therapeutics®, Inc. Cambridge, MA 02142

VAFSEO® is a registered trademark of Akebia Therapeutics, Inc.
©2024 Akebia Therapeutics, Inc. All rights reserved.

Version No. 1

MEDICATION GUIDE

VAFSEO® (VAFF-see-oh)
(vadadustat)
tablets, for oral use

What is the most important information I should know about VAFSEO?

VAFSEO may cause serious side effects, including:

- Increased risk of death, heart attack, stroke, and blood clots. These risks may happen if you are treated with VAFSEO to increase red blood cells (RBCs) to near the same level found in healthy people. These risks may be increased if you have heart or blood vessel problems, or problems with blood flow to your brain (cerebrovascular disease). Blood clots can form in the blood vessels (veins), including your legs (deep vein thrombosis or DVT), lungs (pulmonary embolism or PE), and in your dialysis access (vascular access thrombosis or VAT).
  Get medical help right away if you get any of the following signs or symptoms:
  - chest pain
  - trouble breathing or shortness of breath
  - cold sweat
  - sudden numbness or weakness in your face, arm or leg, especially on one side of your body
  - sudden confusion, trouble speaking, or trouble understanding others’ speech
  - sudden trouble seeing
  - sudden trouble walking, dizziness, loss of balance or coordination
  - loss of consciousness (fainting)
  - severe headache
  - pain in your legs, with or without swelling
  - a cool or pale arm or leg
  - changes to your dialysis access site, including swelling or discoloration near the site
  - do not feel a vibration (“thrill”) over the dialysis access area

See “What are the possible side effects of VAFSEO?” for more information about side effects.
If you decide to take VAFSEO, your healthcare provider should prescribe the lowest dose of VAFSEO that is necessary to reduce your chance of needing red blood cell transfusions.

What is VAFSEO?

VAFSEO is a prescription medicine used to treat anemia caused by chronic kidney disease (CKD) in adults on dialysis for at least 3 months. People with anemia have a lower-than-normal number of red blood cells (RBCs). VAFSEO works by increasing a protein called erythropoietin to help your body make more RBCs. VAFSEO is used to reduce or avoid the need for RBC transfusions.
If your hemoglobin level stays too high or if your hemoglobin goes up too quickly, this may lead to serious health problems which may result in death. These serious health problems may happen if you take VAFSEO, even if you do not have an increase in your hemoglobin levels.
VAFSEO has not been proven to improve quality of life, tiredness (fatigue), or well-being.

VAFSEO should not be used:

- in place of emergency treatment for anemia (red blood cell transfusions).
- for the treatment of anemia that is caused by CKD in people who are not on dialysis.

It is not known if VAFSEO is safe and effective in children.

Who should not take VAFSEO?

Do not take VAFSEO if you:

- are allergic to VAFSEO or to any of its ingredients. See the end of this Medication Guide for a complete list of ingredients in VAFSEO.
- have high blood pressure that is not controlled (uncontrolled hypertension).

Before taking VAFSEO, tell you healthcare provider about all of your medical conditions, including if you:

- have heart disease.
- have had a stroke.
- have liver problems.
- have high blood pressure.
- have had a seizure.
- have a history of damage, such as ulcers, to the lining of the esophagus, stomach, or intestine.
- smoke tobacco or drink alcohol.
- have cancer.
- are pregnant or plan to become pregnant. It is not known if VAFSEO may harm your unborn baby. Talk to your healthcare provider if you become pregnant or think you may be pregnant during treatment with VAFSEO.
- are breastfeeding or plan to breastfeed. It is not known if VAFSEO passes into breast milk. Do not breastfeed during treatment with VAFSEO and for 2 days after your final dose.

Tell your healthcare provider about all the medicines you take, including prescription and over-the-counter medicines, vitamins, and herbal supplements.

- Especially tell your healthcare provider if you take iron supplements, products containing iron or phosphate binders by mouth. These products affect how VAFSEO works and should not be taken at the same time you take VAFSEO. Ask your healthcare provider if you are not sure if you take any of these products. See “How should I take VAFSEO?” for more information.

How should I take VAFSEO?

- Take VAFSEO exactly as your healthcare provider tells you to take it.
- Do not change your dose unless your healthcare provider tells you to.
- You may take VAFSEO with or without food.
- VAFSEO tablets should be swallowed whole. Tablets should not be cut, crushed, or chewed.
- VAFSEO can be taken at any time of the day, including before, during, or after dialysis.
- Take VAFSEO at least 1 hour before you take any of the following:
  - iron supplements
  - products containing iron
  - phosphate binders that contain iron
- Take VAFSEO at least 1 hour before or 2 hours after taking the following:
  - phosphate binders that do not contain iron
- If you miss a dose of VAFSEO, take it as soon as you remember during the same day and then take the next dose at the usual time the next day. Do not take more than 1 dose a day.
- Tell your healthcare provider right away if you take more than your prescribed dose of VAFSEO.
- Your healthcare provider will do certain blood tests before you start VAFSEO and during treatment as needed.
- Your healthcare provider may change your dose of VAFSEO based on the results of your blood tests.

What are the possible side effects of VAFSEO?

VAFSEO may cause serious side effects, including:

- See “What is the most important information I should know about VAFSEO?”
- Liver problems. VAFSEO may cause changes in blood liver tests, which may be a sign of liver injury. Your healthcare provider will do blood liver tests before starting treatment with VAFSEO, monthly for the first 6 months and then as needed. Your healthcare provider may stop treatment with VAFSEO if you have changes in your blood liver tests. Tell your healthcare provider if you get any of these symptoms:
  - tiredness
  - pain in your right upper stomach area (abdomen)
  - yellowing of your skin or the white part of your eyes
  - loss of appetite
  - dark urine
- High blood pressure. VAFSEO may cause you to develop new or worsening high blood pressure. It is important to check your blood pressure regularly and to follow any instructions from your healthcare provider about how to control your blood pressure. Tell your healthcare provider about any changes in your blood pressure.
- Seizures. Seizures have happened in people treated with VAFSEO. Tell your healthcare provider about new onset of seizures, change in how often you have seizures, or if you get any of the following signs or symptoms that a seizure may happen: headache, irritability, fear, confusion, or unusual feelings.
- Damage, such as ulcers, to the lining of the esophagus, stomach, or intestines (gastrointestinal erosion). Your risk of gastrointestinal erosion may increase if you have a history of gastrointestinal erosion, stomach ulcers (peptic ulcer disease), use certain medicines that increase the risk of gastrointestinal erosion, or currently smoke tobacco or drink alcohol. Get medical care right away if you get any of these signs or symptoms:
  - stomach-area (abdominal) discomfort or pain
  - black, tarry stools
  - nausea or vomiting
  - trouble swallowing
  - blood in your vomit or stool
  - pain in your throat or chest
- Cancer. Cancer was observed in people treated with VAFSEO. Talk to your healthcare provider if you have any concerns about cancer.

The most common side effects of VAFSEO include:

- high blood pressure
- diarrhea

These are not all the possible side effects of VAFSEO. For more information, ask your healthcare provider or pharmacist.

Call your doctor for medical advice about side effects. You may report side effects to FDA at 1-800-FDA-1088.

How should I store VAFSEO?

- Store VAFSEO at room temperature between 68℉ to 77℉ (20℃ to 25℃).

Keep VAFSEO and all medicines out of the reach of children.

General information about the safe and effective use of VAFSEO.

Medicines are sometimes prescribed for purposes other than those listed in a Medication Guide. Do not use VAFSEO for a condition for which it was not prescribed. Do not give VAFSEO to other people, even if they have the same symptoms that you have. It may harm them. You can ask your pharmacist or healthcare provider for information about VAFSEO that is written for health professionals.

What are the ingredients in VAFSEO?

Active ingredient: vadadustat.

Inactive ingredients: colloidal silicon dioxide, hydroxypropyl methylcellulose, magnesium stearate, microcrystalline cellulose, and sodium starch glycolate.

The tablet film-coating contains polyvinyl alcohol, polyethylene glycol (PEG) and talc.

Colorants include:

150 mg tablets: titanium dioxide

300 mg tablets: titanium dioxide and yellow iron oxide

450 mg tablets: titanium dioxide, iron oxide red and ferrosoferric oxide

Manufactured for: Akebia Therapeutics®, Inc., Cambridge, MA 02142

VAFSEO® is a registered trademark of Akebia Therapeutics, Inc.

©2024 Akebia Therapeutics, Inc. All rights reserved.

For more information, go to www.VAFSEO.com or call 1-844-445-3799.

v1

This Medication Guide has been approved by the U.S. Food and Drug Administration.

Issued: 03/2024